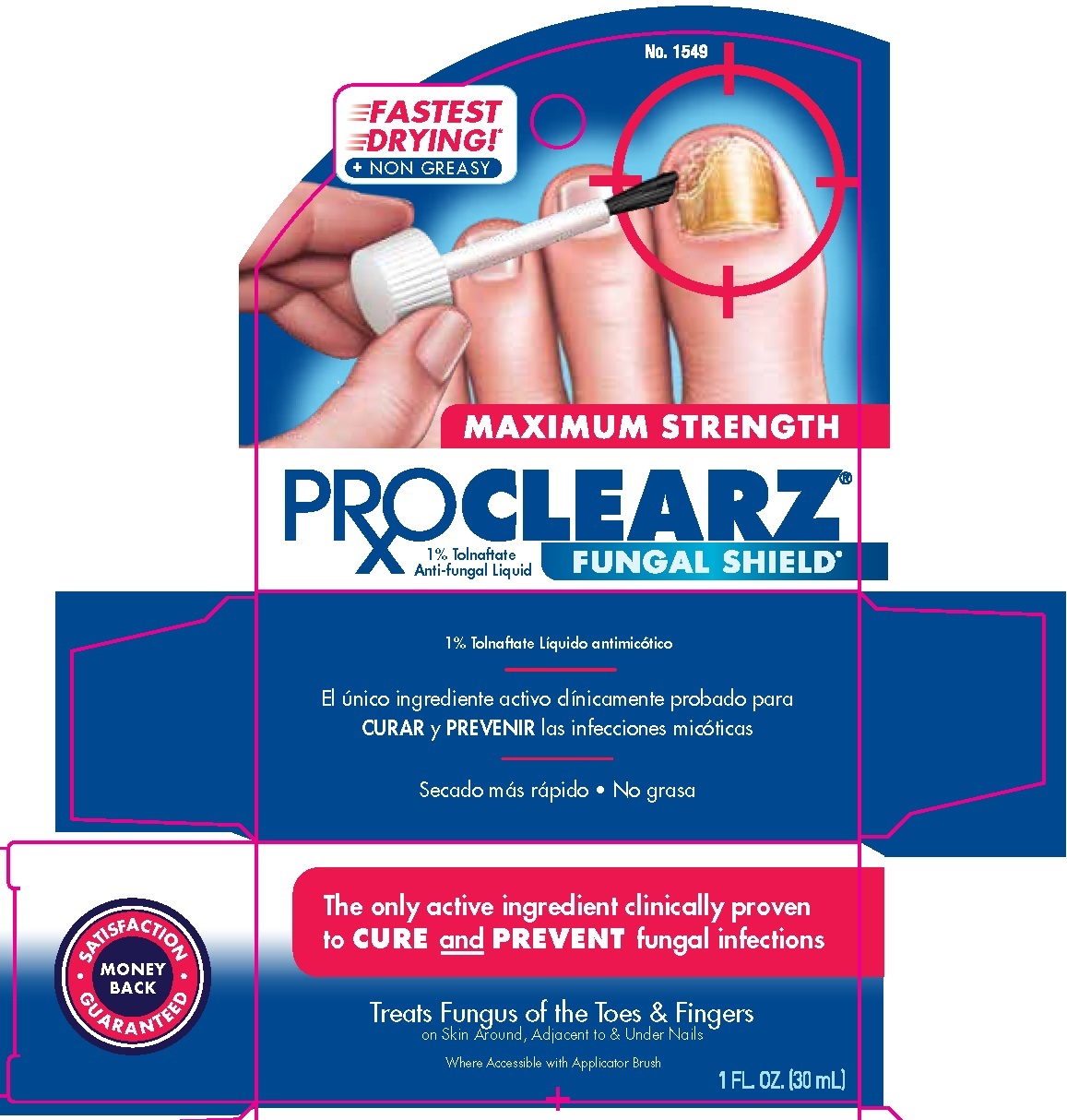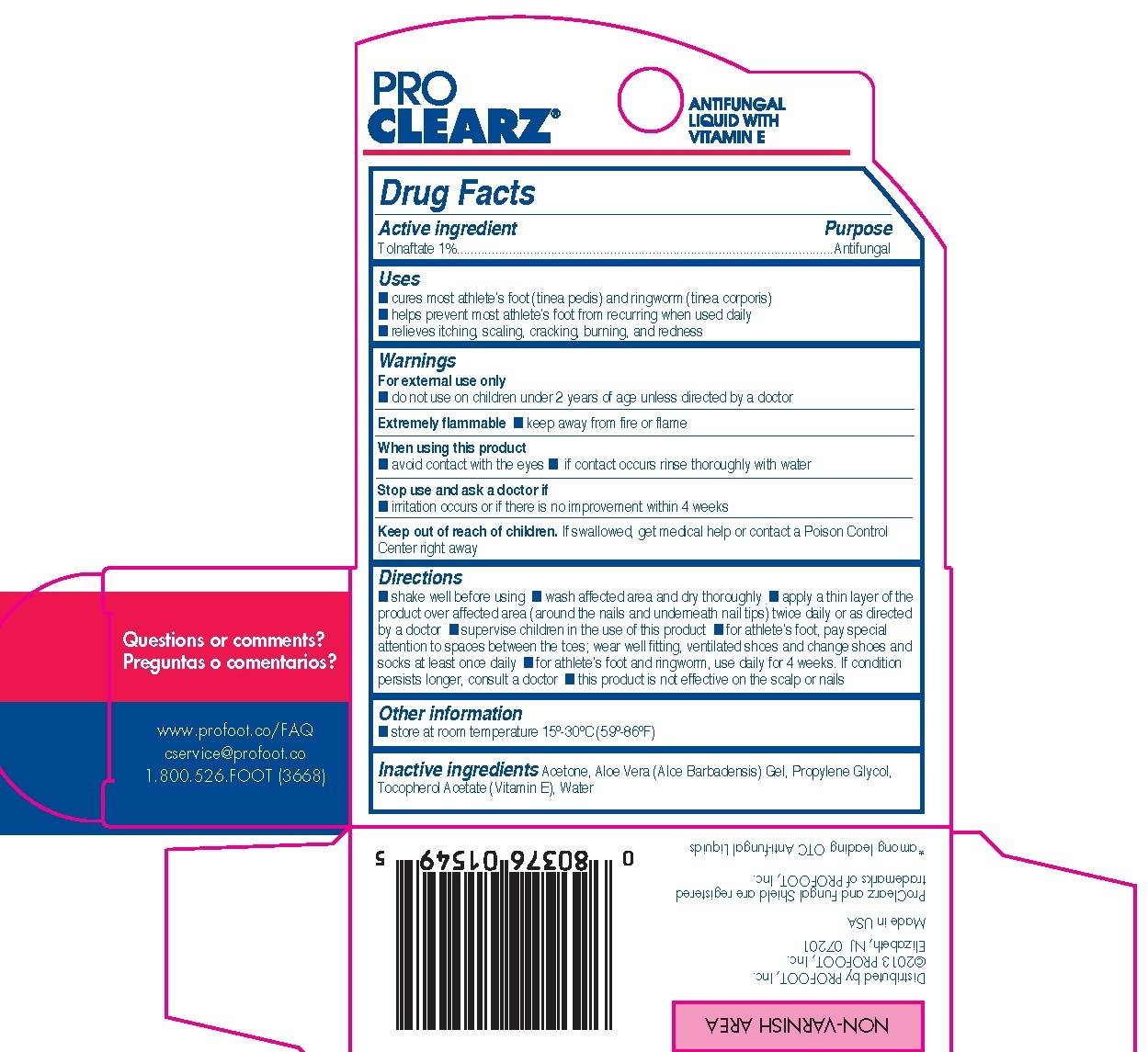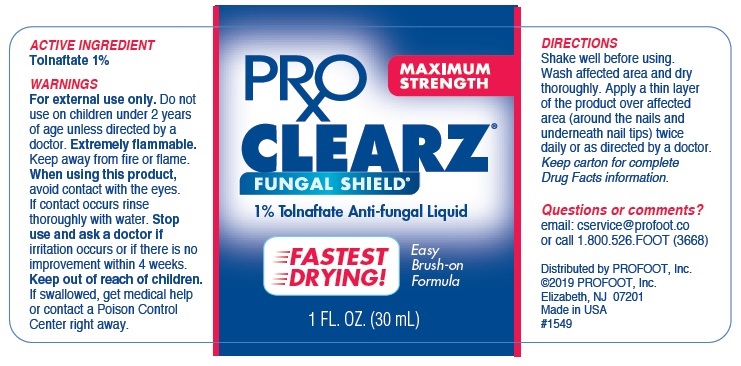 DRUG LABEL: ProClearz
NDC: 29784-181 | Form: SOLUTION
Manufacturer: Rooftop Consumer Health, Inc.
Category: otc | Type: HUMAN OTC DRUG LABEL
Date: 20260302

ACTIVE INGREDIENTS: TOLNAFTATE 10 mg/1 mL
INACTIVE INGREDIENTS: ACETONE; ALOE VERA LEAF; .ALPHA.-TOCOPHEROL ACETATE; PROPYLENE GLYCOL; WATER

ProClearz Maximum Strength Fungal Sheild Anti-Fungal Brush-On Solution

Active Ingredient

Tolnaftate 1%

Purpose

Anti-fungal

Uses

- cures most athlete's foot (tinea pedis) and ringworm (tinea corporis)
- helps prevent most athlete's foot from recurring when used daily
- relieves itching, scaling, cracking, burning, and redness

Warnings

For external use only

- do not use on children under 2 years of age unless directed by a doctor

GENERAL PRECAUTIONS

Extremely flammable

- keep away from fire or flame

When using this product

- avoid contact with the eyes
- if contact occurs rinse thoroughly with water

Stop use and ask a doctor if

- irritation occurs or if there is no improvement in 4 weeks

KEEP OUT OF REACH OF CHILDREN

If swallowed, get medical help or contact a Poison Control Center right away Keep out of reach of children.

Directions

■ shake well before using ■ wash affected area and dry thoroughly ■ apply a thin layer of the product over affected area (around the nails and underneath nail tips) twice daily or as directed by a doctor ■ supervise children in the use of this product ■ for athlete’s foot, pay special attention to spaces between the toes; wear well fitting, ventilated shoes and change shoes and socks at least once daily ■ for athlete’s foot and ringworm, use daily for 4 weeks. If condition persists longer, consult a doctor ■ this product is not effective on the scalp or nails

Other Information

- store at room temperature 15º-30ºC (59º-86ºF)

Inactive ingredients

Acetone, Aloe Vera (Aloe Barbadensis) Gel, Propylene Glycol, Tocopherol Acetate (Vitamin E), Water